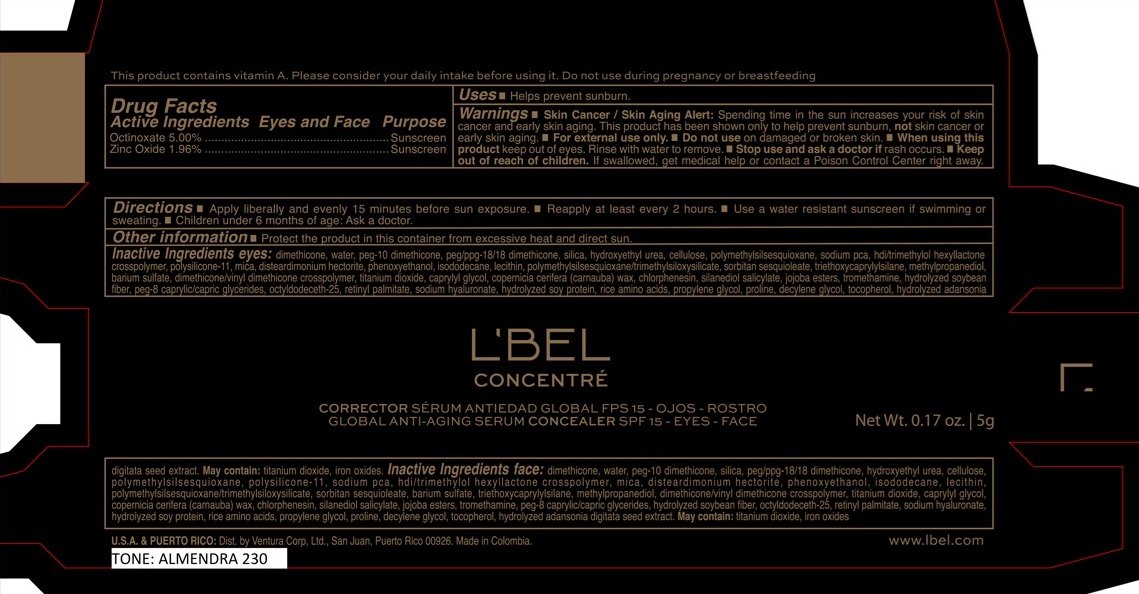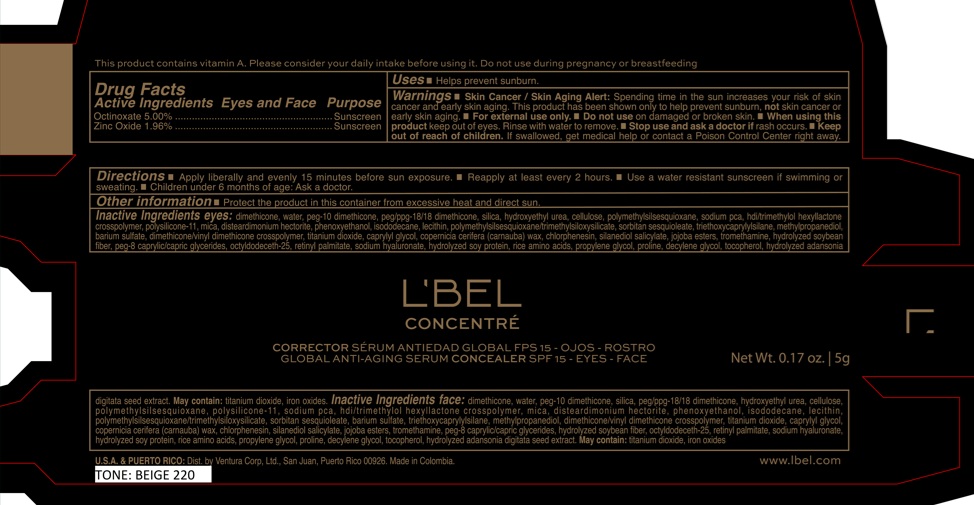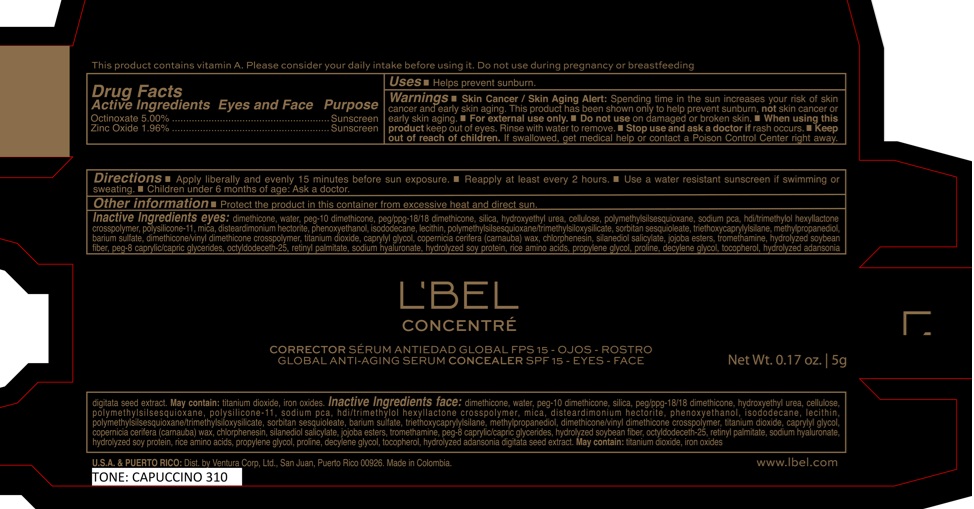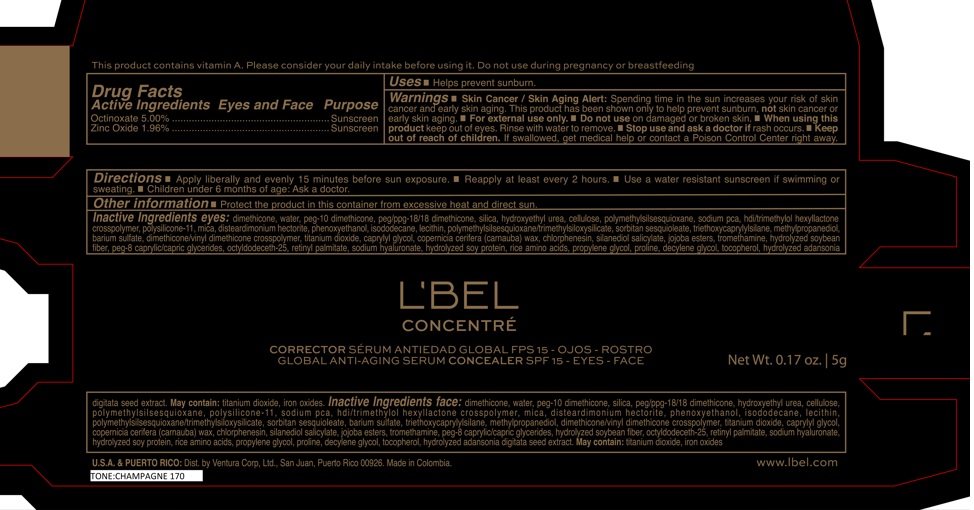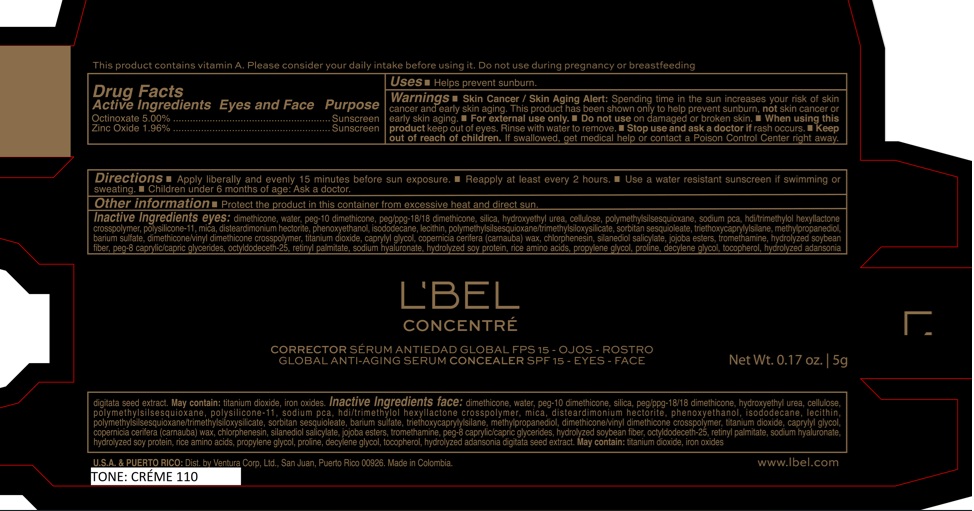 DRUG LABEL: LBEL CONCENTRE GLOBAL ANTI AGING SERUM CONCEALER SPF 15 EYES FACE ALMENDRA 230
NDC: 14141-366 | Form: EMULSION
Manufacturer: BEL STAR S.A.
Category: otc | Type: HUMAN OTC DRUG LABEL
Date: 20250127

ACTIVE INGREDIENTS: ZINC OXIDE 19.6 mg/1 g; OCTINOXATE 50 mg/1 g
INACTIVE INGREDIENTS: PROLINE; PEG/PPG-18/18 DIMETHICONE; HDI/TRIMETHYLOL HEXYLLACTONE CROSSPOLYMER; DISTEARDIMONIUM HECTORITE; CARNAUBA WAX; MICA; PEG-10 DIMETHICONE (600 CST); SODIUM PCA; LECITHIN, SUNFLOWER; TRIETHOXYCAPRYLYLSILANE; OCTYLDODECETH-25; PROPYLENE GLYCOL; POWDERED CELLULOSE; SORBITAN SESQUIOLEATE; SILANEDIOL SALICYLATE; WATER; SODIUM HYALURONATE; HYDROLYZED SOY PROTEIN (ENZYMATIC; 2000 MW); JOJOBA OIL, RANDOMIZED; PEG-8 CAPRYLIC/CAPRIC GLYCERIDES; TROMETHAMINE; METHYLPROPANEDIOL; RETINYL PALMITATE; SILICON DIOXIDE; POLYMETHYLSILSESQUIOXANE; DIMETHICONE/VINYL DIMETHICONE CROSSPOLYMER (SOFT PARTICLE); ISODODECANE; DIMETHICONE; HYDROXYETHYL UREA; PHENOXYETHANOL; POLYMETHYLSILSESQUIOXANE/TRIMETHYLSILOXYSILICATE; BARIUM SULFATE; TITANIUM DIOXIDE; CAPRYLYL GLYCOL; RICE AMINO ACIDS; TOCOPHEROL; IRON OXIDES; CHLORPHENESIN; DECYLENE GLYCOL

LBEL CONCENTRE GLOBAL ANTI AGING SERUM CONCEALER SPF 15 EYES FACE

Active Ingredients

Octinoxate 5.00%

Zinc Oxide 1.96%

Purpose

Sunscreen

Uses

- Helps prevent sunburn.

Warnings

- Skin Cancer / Skin Aging Alert: Spending time in the sun increases your risk of skin cancer and early skin aging. This product has been shown only to help prevent sunburn, not skin cancer or early skin aging.
- For external use only.

Do not use

on damaged or broken skin.

When using this product

keep out of eyes. Rinse with water to remove.

Stop use and ask a doctor if

rash occurs.

Keep out of reach of children.

If swallowed, get medical help or contact a Poison Control Center right away.

Directions

- Apply liberally and evenly 15 minutes before sun exposure.
- Reapply at least every 2 hours
- Use a water resistant sunscreen if swimming or sweating.
- Children under 6 months of age: Ask a doctor

Other information

- Protect the product in this container from excessive heat and direct sun.

Inactive Ingredients

Inactive ingredients eyes: dimethicone, water, peg-10 dimethicone, peg/ppg-18/18 dimethicone, silica, hydroxyethyl urea, cellulose, polymethylsilsesquioxane, sodium pca, hdi/trimethylol hexyllactone crosspolymer, polysilicone-11, mica, disteardimonium hectorite, phenoxyethanol, isododecane, lecithin, polymethylsilsesquioxane/trimethylsiloxysilicate, sorbitan sesquioleate, triethoxycaprylylsilane, methylpropanediol, barium sulfate, dimethicone/vinyl dimethicone crosspolymer, titanium dioxide, caprylyl glycol, copernicia cerifera (carnauba) wax, chlorphenesin, silanediol salicylate, jojoba esters, tromethamine, hydrolyzed soybean fiber, peg-8 caprylic/capric glycerides, octyldodeceth-25, retinyl palmitate, sodium hyaluronate, hydrolyzed soy protein, rice amino acids, propylene glycol, proline, decylene glycol, tocopherol, hydrolyzed adansonia digitata seed extract.
May contain: titanium dioxide, iron oxides.

Inactive ingredients face: dimethicone, water, peg-10 dimethicone, silica, peg/ppg-18/18 dimethicone, hydroxyethyl urea, cellulose, polymethylsilsesquioxane, polysilicone-11, sodium pca, hdi/trimethylol hexyllactone crosspolymer, mica, disteardimonium hectorite, phenoxyethanol, isododecane, lecithin, polymethylsilsesquioxane/trimethylsiloxysilicate, sorbitan sesquioleate, barium sulfate, triethoxycaprylylsilane, methylpropanediol, dimethicone/vinyl dimethicone crosspolymer, titanium dioxide, caprylyl glycol, copernicia cerifera (carnauba) wax, chlorphenesin, silanediol salicylate, jojoba esters, tromethamine, peg-8 caprylic/capric glycerides, hydrolyzed soybean fiber, octyldodeceth-25, retinyl palmitate, sodium hyaluronate, hydrolyzed soy protein, rice amino acids, propylene glycol, proline, decylene glycol, tocopherol, hydrolyzed adansonia digitata seed extract.
May contain: titanium dioxide, iron oxides